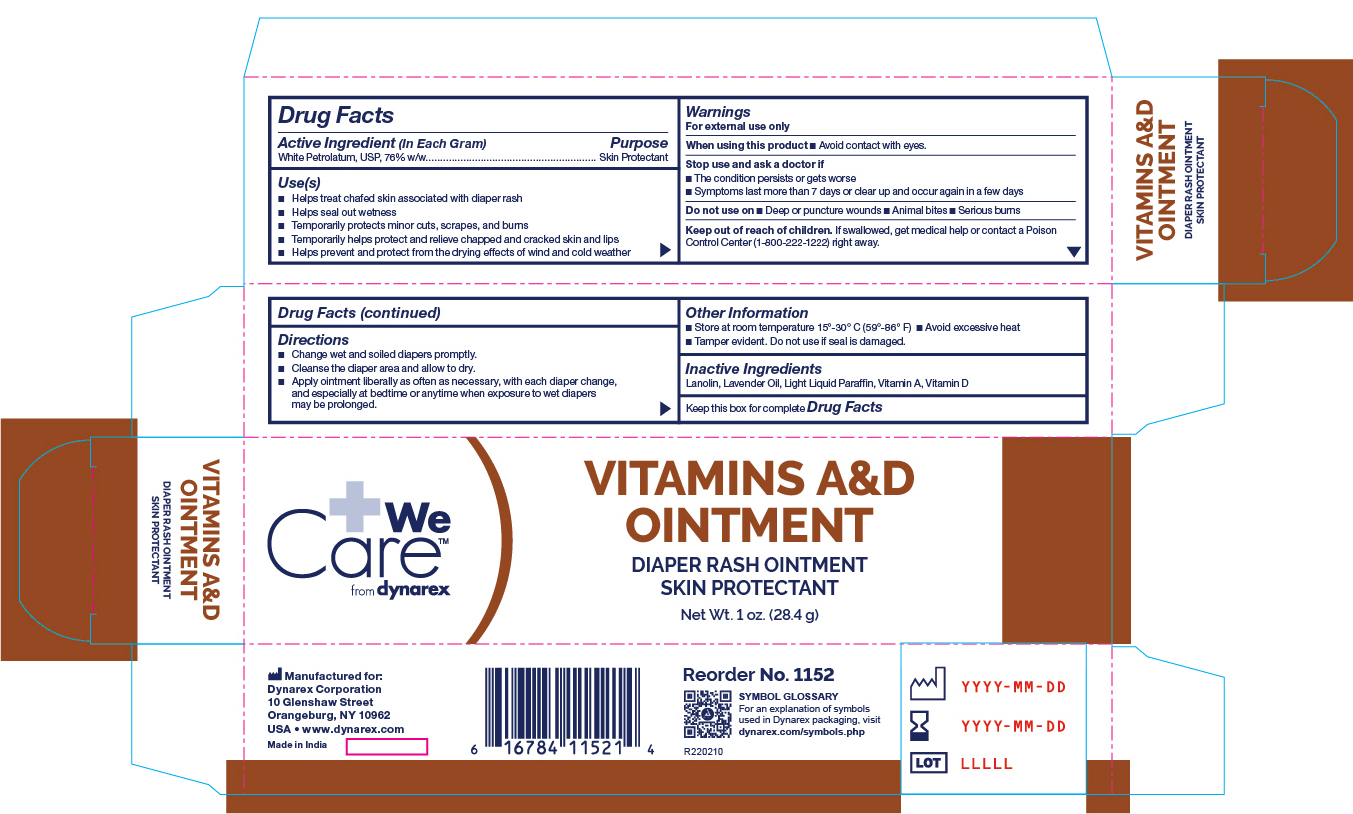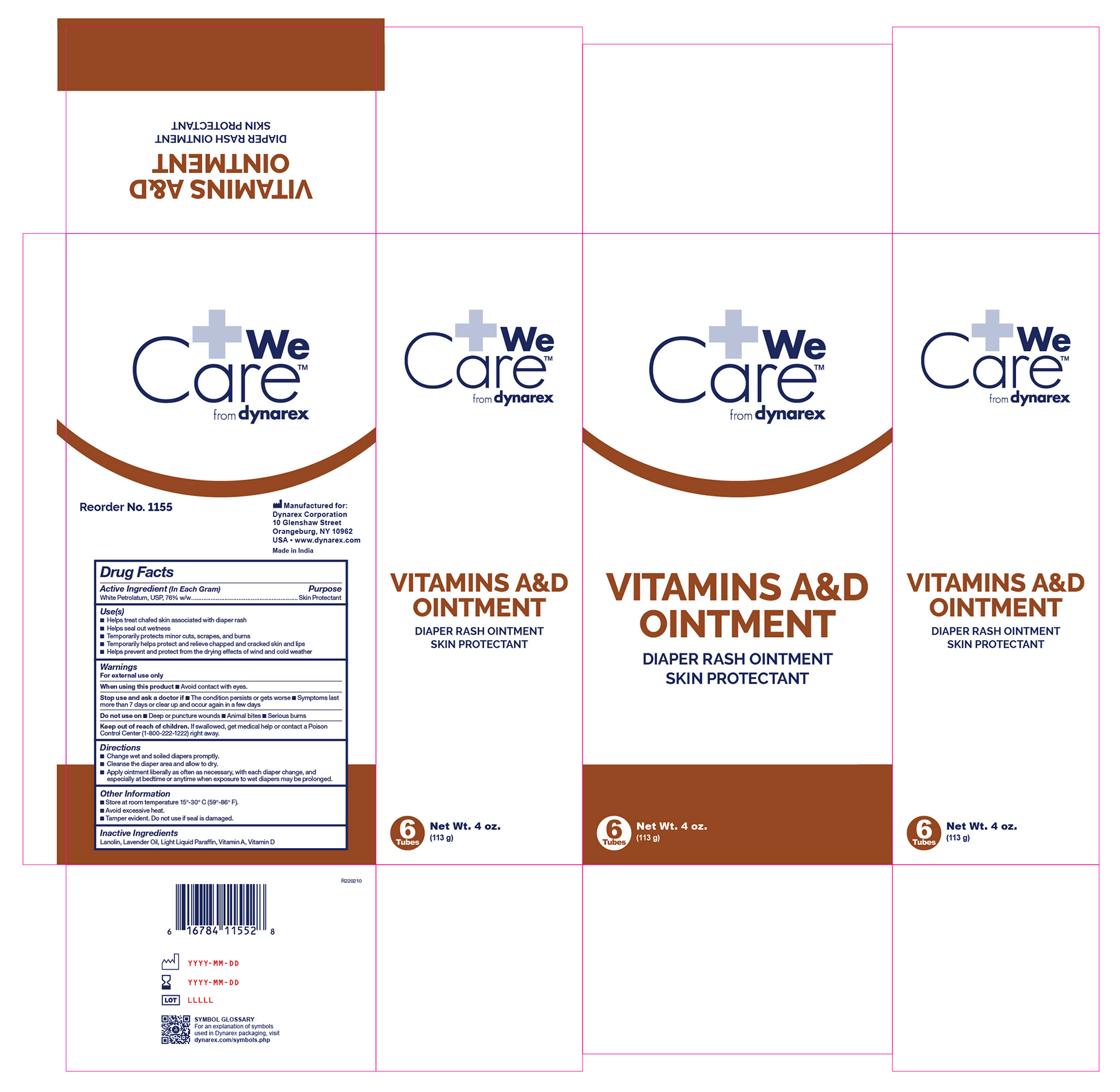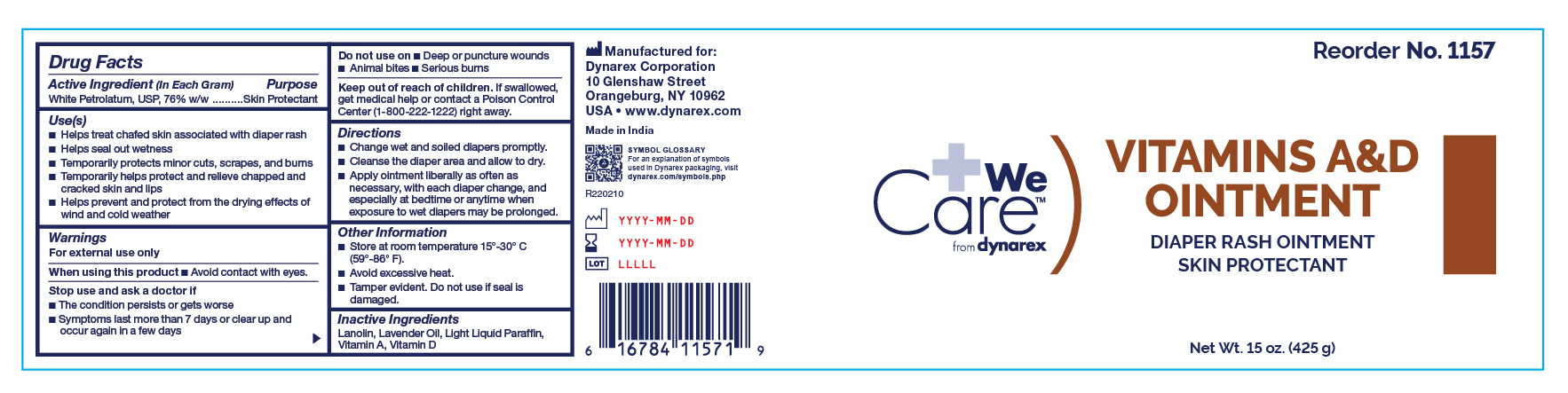 DRUG LABEL: Vitamin A D
NDC: 67777-214 | Form: OINTMENT
Manufacturer: Dynarex Corporation
Category: otc | Type: HUMAN OTC DRUG LABEL
Date: 20241120

ACTIVE INGREDIENTS: PETROLATUM 0.76 g/1 g
INACTIVE INGREDIENTS: LAVENDER OIL; VITAMIN D; VITAMIN A PALMITATE; LANOLIN; LIGHT MINERAL OIL

1152 - Vitamins A&D Ointment, 1 oz tube NDC 67777-214-04
1155 - Vitamins A&D Ointment, 4 oz tube NDC 67777-214-01
1157 - Vitamins A&D Ointment, 15 oz Jar, NDC 67777-214-02

Active Ingredient Purpose

White Petrolatum USP (76%) Skin Protectant

Uses: Vitamin_A_D

- Helps treat and prevent diaper rash
- Helps seal out wetness

- Temporarily protects minor * cuts * scrapes * burns
- Temporarily helps protect and help relieve chapped and cracked skin and lips
- Helps prevent and protect from the drying effects of wind and cold weather
- Helps prevent and protect chafed skin or minor skin irritations associated with diaper rash
- With each diaper change, especially at bedtime when exposure to wet diapers may be prolonged

Warnings:

For External Use Only

Do Not Get In Eyes

Stop use and ask a doctor if:

- If condition worsens
- symptoms last more than 7 days or clear up and occur again in a few days

Do not use on:

- Deep or puncture wounds
- animal bites
- serious burns

Keep out of reach of children

- If swallowed, get medical help or contact a Poison Control Center right away.

Directions for diaper rash:

- Change wet and soiled diapers promptly
- Cleanse the diaper area and allow to dry
- Apply as needed

Other information:

- Store at room temperature 15 deg C to 30 deg C 59 deg F to 86 deg F
- Avoid excessive heat

Inactive Ingredients

Inactive Ingredients: Lanolin, Lavender Oil, Light Liquid Paraffin, Vitamin A, Vitamin D

Indications and Usage

A skin protectant for the treatment of diaper rash, minor cuts, scrapes, burns and to help relieve chapped and cracked skin and lips.